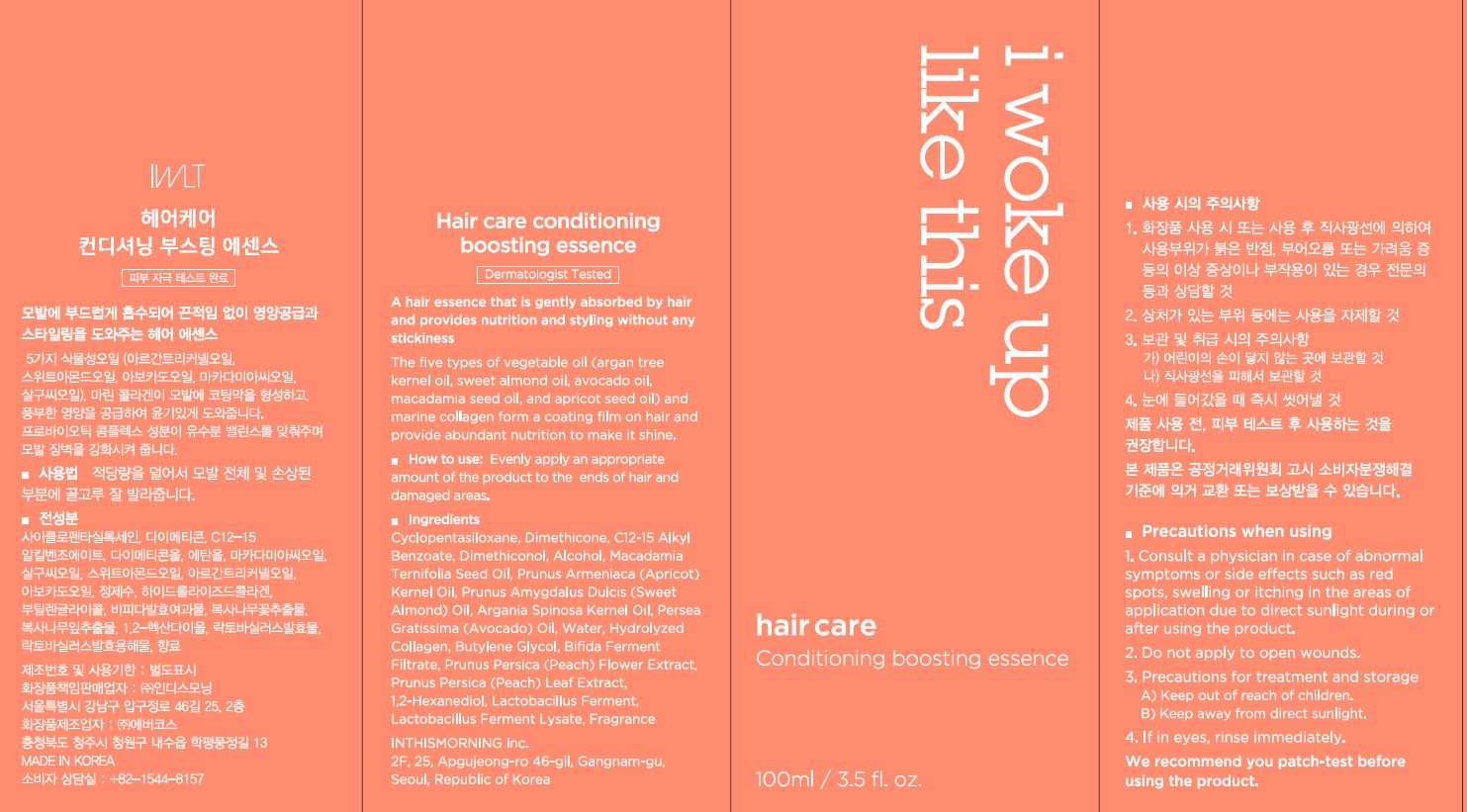 DRUG LABEL: Hair care conditioning Boosting essence
NDC: 71217-0069 | Form: LIQUID
Manufacturer: inthismorning co ltd
Category: otc | Type: HUMAN OTC DRUG LABEL
Date: 20230201

ACTIVE INGREDIENTS: ARGAN OIL 0.001 g/100 mL
INACTIVE INGREDIENTS: WATER; DIMETHICONE

Drug Facts

ACTIVE INGREDIENT

Argania Spinosa Kernel Oil

INACTIVE INGREDIENT

Cyclopentasiloxane
Dimethicone
C12-15 Alkyl Benzoate
Dimethiconol
Alcohol
Macadamia Ternifolia Seed Oil
Prunus Armeniaca (Apricot) Kernel Oil
Prunus Amygdalus Dulcis (Sweet Almond) Oil
Persea Gratissima (Avocado) Oil
Water
Hydrolyzed Collagen
Butylene Glycol
Bifida Ferment Filtrate
Prunus Persica (Peach) Flower Extract
Prunus Persica (Peach) Leaf Extract
1,2-Hexanediol
Lactobacillus Ferment
Lactobacillus Ferment Lysate
Fragrance

PURPOSE

hair care

keep out or reach of the children

INDICATIONS AND USAGE

evenly apply an appropriate amount of the product to the ends of hair and damaged areas

WARNINGS

This product is for exeternal use only. Do not use for internal use
Storage and handling precautions
If possible, avoid direct sunlight and store in cool and area of low humidity in order to maintain the quality of the product and avoid misuse
Avoid placing the product near fire and store out in reach of children

- consult a physician in case of abnormal symptoms, such as red spots, swelling or itching, or side effects in the areas of application due to direct light during or after using the product

- do not use on wounded area

DOSAGE AND ADMINISTRATION

for external use only